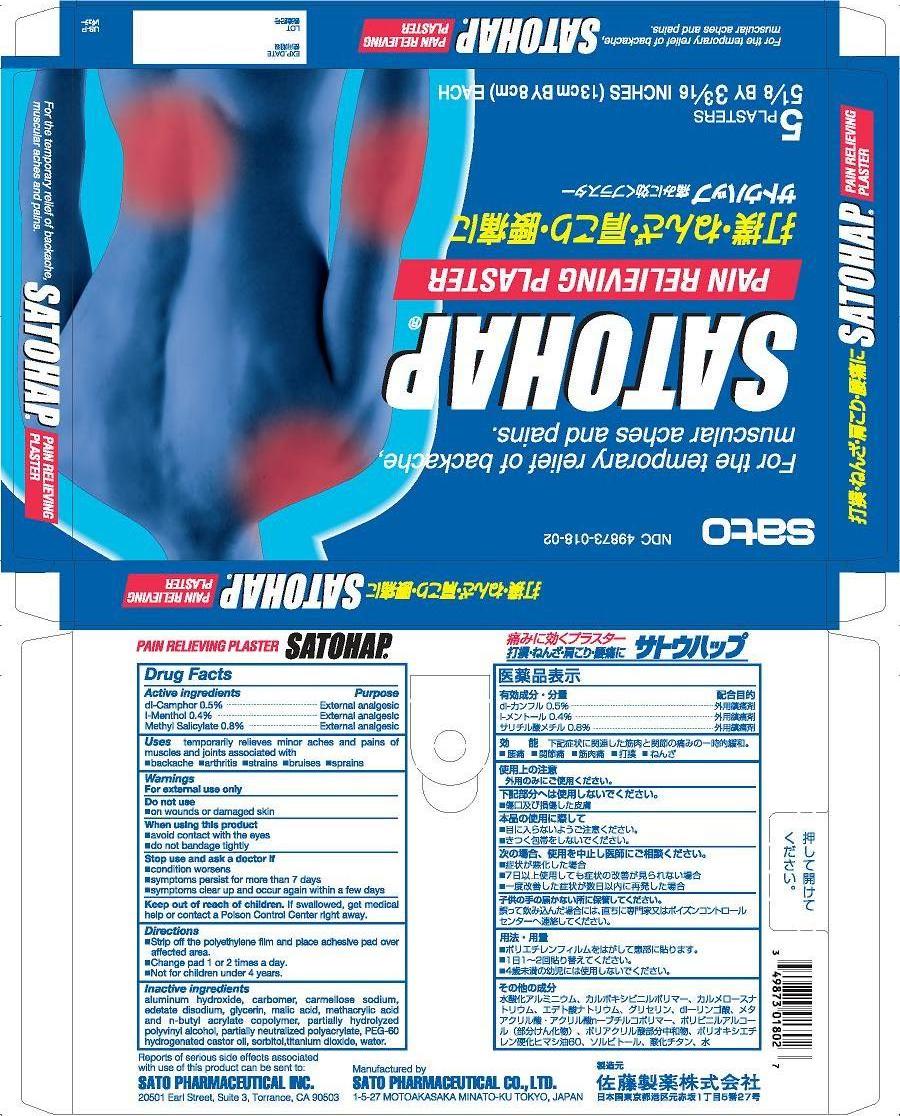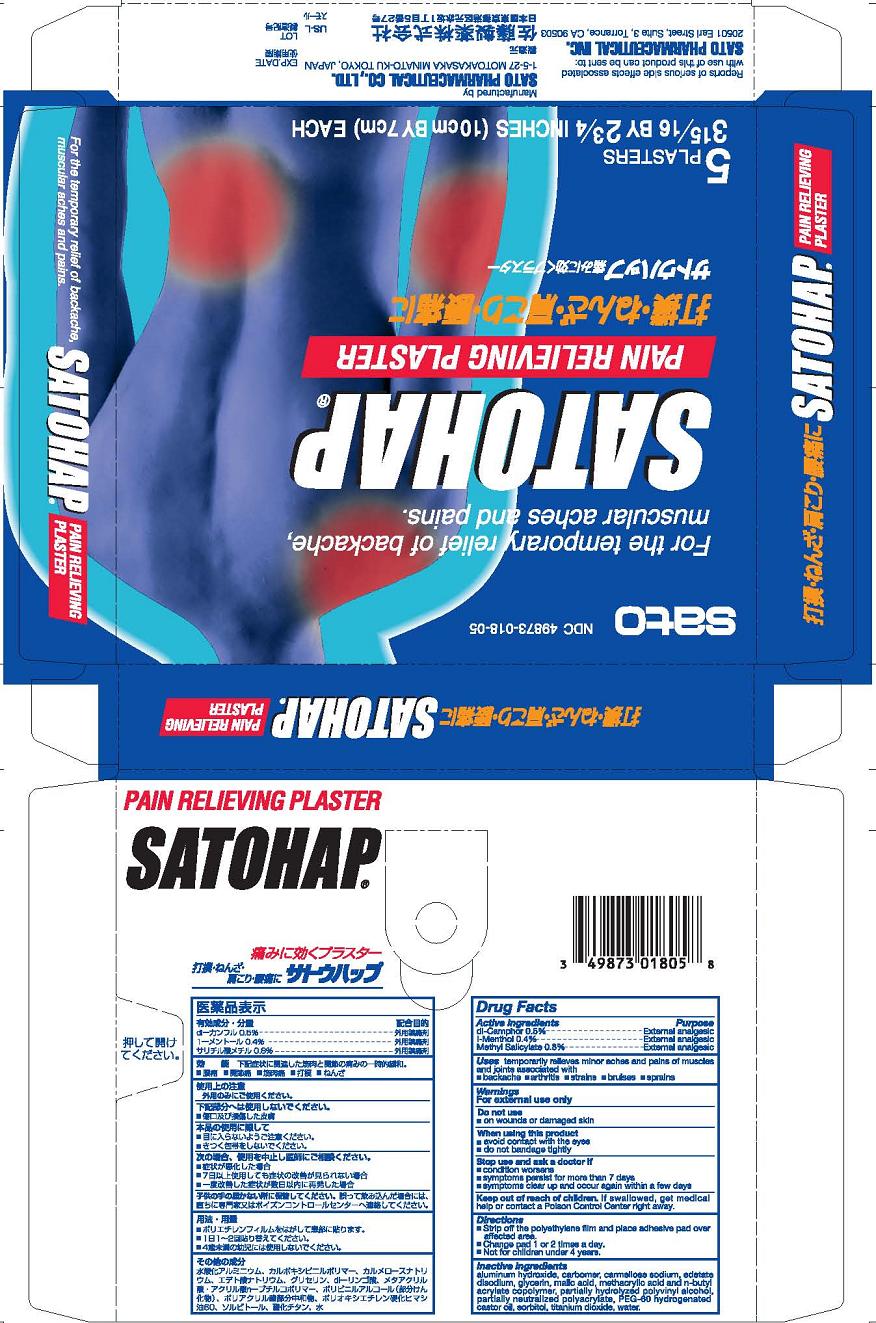 DRUG LABEL: Satohap
NDC: 49873-018 | Form: PATCH
Manufacturer: Sato Pharmaceutical Co., Ltd.
Category: otc | Type: HUMAN OTC DRUG LABEL
Date: 20231110

ACTIVE INGREDIENTS: CAMPHOR (SYNTHETIC) 5 mg/1 1; LEVOMENTHOL 4 mg/1 1; METHYL SALICYLATE 8 mg/1 1
INACTIVE INGREDIENTS: POLYVINYL ALCOHOL; SORBITOL; GLYCERIN; TITANIUM DIOXIDE; EDETATE DISODIUM; ALGELDRATE; MALIC ACID; WATER; POLYOXYL 60 HYDROGENATED CASTOR OIL; ACRYLIC ACID/SODIUM ACRYLATE COPOLYMER (1:1; 600 MPA.S AT 0.2%); CARBOXYMETHYLCELLULOSE SODIUM; BUTYL ACRYLATE/METHACRYLIC ACID COPOLYMER (2% METHACRYLIC ACID); CARBOMER INTERPOLYMER TYPE B (ALLYL PENTAERYTHRITOL CROSSLINKED)

Satohap Plaster

Active ingredients
dl-Camphor 0.5%
l-Menthol 0.4%
Methyl Salicylate 0.8%

Purpose
dl-Camphor External analgesic
l-Menthol External analgesic
Methyl Salicylate External analgesic

INDICATIONS AND USAGE

Uses temporary relieves minor aches and pains of muscles and joints associated with
■ simple backache ■ arthritis ■ strains ■ bruises ■ sprains

Warnings
For external use only

Do not use
■ on wounds or on damaged skin

When using this product
■ avoid contact with the eyes
■ do not bandage tightly

Stop use and ask a doctor if
■ condition worsens
■ symptoms persist for more than 7 days
■ symptoms clear up and occur again withn a few days

Keep out of reach of children. If swallowed, get medical help or contact a Poison Control Center right away.

Directions
■ Strip off the polyethylene film and place adhesive pad over affected area.
■ Change pad 1 or 2 times a day
■ Not for children under 4 years.

Inactive ingredients
aluminum hydroxide gel, carbomer, carmellose sodium, edetate disodium, glycerin, malic acid, methacrylic acid and n-butyl acrylate copolymer, partially hydrolyzed polyvinyl alcohol, partially neutralized polyacrylate, PEG 60 hydrogenated castor oil, sorbitol, titanium dioxide, water.